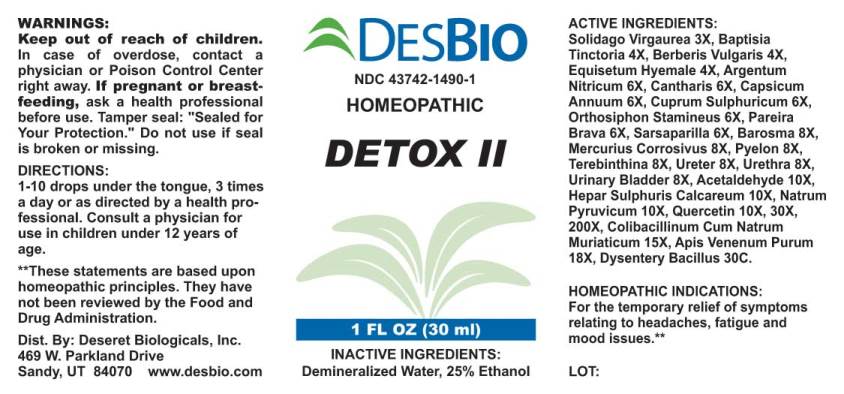 DRUG LABEL: Detox
NDC: 43742-1490 | Form: LIQUID
Manufacturer: Deseret Biologicals, Inc.
Category: homeopathic | Type: HUMAN OTC DRUG LABEL
Date: 20211005

ACTIVE INGREDIENTS: SOLIDAGO VIRGAUREA FLOWERING TOP 3 [hp_X]/1 mL; BAPTISIA TINCTORIA ROOT 4 [hp_X]/1 mL; BERBERIS VULGARIS ROOT BARK 4 [hp_X]/1 mL; EQUISETUM HYEMALE 4 [hp_X]/1 mL; SILVER NITRATE 6 [hp_X]/1 mL; LYTTA VESICATORIA 6 [hp_X]/1 mL; CAPSICUM 6 [hp_X]/1 mL; CUPRIC SULFATE 6 [hp_X]/1 mL; ORTHOSIPHON ARISTATUS WHOLE 6 [hp_X]/1 mL; CHONDRODENDRON TOMENTOSUM ROOT 6 [hp_X]/1 mL; SMILAX ORNATA ROOT 6 [hp_X]/1 mL; AGATHOSMA BETULINA LEAF 8 [hp_X]/1 mL; MERCURIC CHLORIDE 8 [hp_X]/1 mL; SUS SCROFA RENAL PELVIS 8 [hp_X]/1 mL; TURPENTINE OIL 8 [hp_X]/1 mL; SUS SCROFA URETER 8 [hp_X]/1 mL; SUS SCROFA URETHRA 8 [hp_X]/1 mL; SUS SCROFA URINARY BLADDER 8 [hp_X]/1 mL; ACETALDEHYDE 10 [hp_X]/1 mL; CALCIUM SULFIDE 10 [hp_X]/1 mL; SODIUM PYRUVATE 10 [hp_X]/1 mL; QUERCETIN 10 [hp_X]/1 mL; ESCHERICHIA COLI 15 [hp_X]/1 mL; APIS MELLIFERA VENOM 18 [hp_X]/1 mL; SHIGELLA DYSENTERIAE 30 [hp_C]/1 mL
INACTIVE INGREDIENTS: WATER; ALCOHOL

Drug Facts:

ACTIVE INGREDIENTS:

Solidago Virgaurea 3X, Baptisia Tinctoria 4X, Berberis Vulgaris 4X, Equisetum Hyemale 4X, Argentum Nitricum 6X, Cantharis 6X, Capsicum Annuum 6X, Cuprum Sulphuricum 6X, Orthosiphon Stamineus 6X, Pareira Brava 6X, Sarsaparilla (Smilax Regelii) 6X, Barosma (Betulina) 8X, Mercurius Corrosivus 8X, Pyelon (Suis) 8X, Terebinthina 8X, Ureter (Suis) 8X, Urethra (Suis) 8X, Urinary Bladder (Suis) 8X, Acetaldehyde 10X, Hepar Sulphuris Calcareum 10X, Natrum Pyruvicum 10X, Quercetin 10X, 30X, 200X, Colibacillinum Cum Natrum Muriaticum 15X, Apis Venenum Purum 18X, Dysentery Bacillus 30C.

HOMEOPATHIC INDICATIONS:

For the temporary relief of symptoms relating to headaches, fatigue and mood issues.**

**These statements are based upon traditional homeopathic principles. They have not been reviewed by the Food and Drug Administration.

WARNINGS:

Keep out of reach of children. In case of overdose, contact physician or a Poison Control Center right away.
If pregnant of breast-feeding, seek advice of a health professional before use.
Tamper seal: "Sealed for Your Protection." Do not use if seal is broken or missing.

Keep out of reach of children. In case of overdose, contact physician or a Poison Control Center right away.

DIRECTIONS:

1-10 drops under the tongue, 3 times a day or as directed by a health professional. Consult a physician for use in children under 12 years of age.

HOMEOPATHIC INDICATIONS:

For the temporary relief of symptoms relating to headaches, fatigue and mood issues.**

**These statements are based upon traditional homeopathic principles. They have not been reviewed by the Food and Drug Administration.

INACTIVE INGREDIENTS:

Demineralized water, 25% Ethanol.

QUESTIONS:

Dist. By:
Deseret Biologicals, Inc.
469 W. Parkland Drive
Sandy, UT 84070
www.desbio.com

PACKAGE LABEL DISPLAY:

DESBIO

NDC 43742-1490-1

HOMEOPATHIC

DETOX II

1 FL OZ (30 ml)